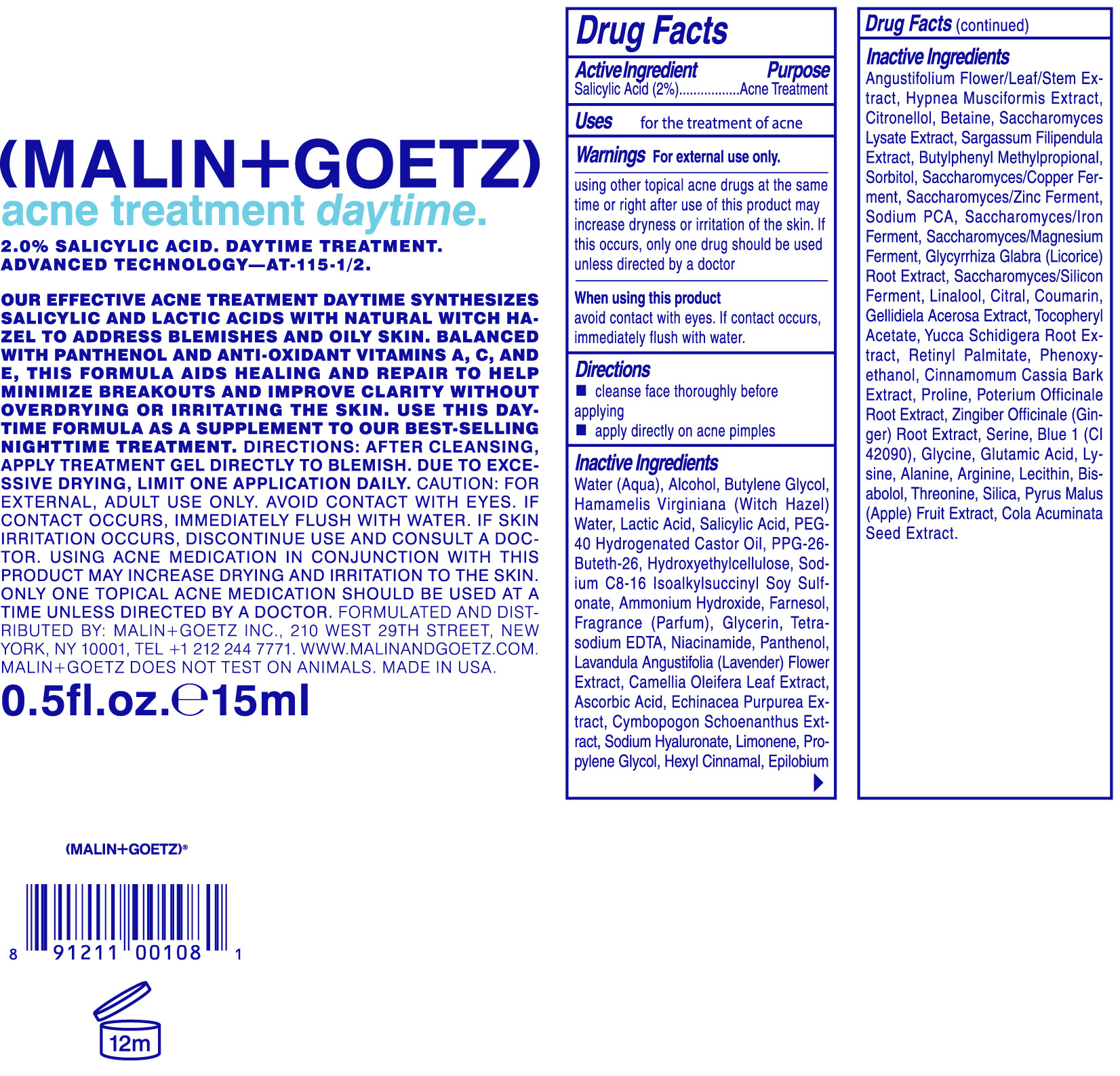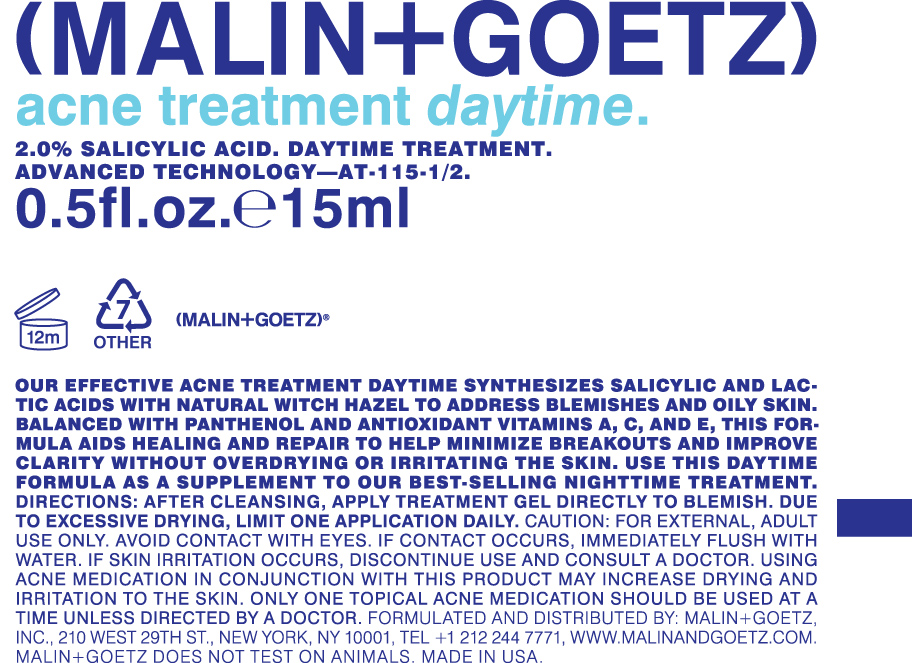 DRUG LABEL: Acne treatment daytime
NDC: 53634-125 | Form: CREAM
Manufacturer: Malin and Goetz Inc
Category: otc | Type: HUMAN OTC DRUG LABEL
Date: 20210126

ACTIVE INGREDIENTS: SALICYLIC ACID 2 g/1 mL
INACTIVE INGREDIENTS: WATER; ALCOHOL; BUTYLENE GLYCOL; HAMAMELIS VIRGINIANA TOP WATER; LACTIC ACID; POLYOXYL 40 HYDROGENATED CASTOR OIL; PPG-26-BUTETH-26; HYDROXYETHYL CELLULOSE (140 CPS AT 5%); AMMONIA; FARNESOL; GLYCERIN; NIACINAMIDE; PANTHENOL; LAVANDULA ANGUSTIFOLIA SUBSP. ANGUSTIFOLIA FLOWER; CAMELLIA OLEIFERA LEAF; ASCORBIC ACID; ECHINACEA PURPUREA; CYMBOPOGON SCHOENANTHUS TOP; HYALURONATE SODIUM; LIMONENE, (+)-; PROPYLENE GLYCOL; .ALPHA.-HEXYLCINNAMALDEHYDE; EPILOBIUM ANGUSTIFOLIUM FLOWERING TOP; HYPNEA MUSCIFORMIS; BETAINE; SACCHAROMYCES LYSATE; SARGASSUM FILIPENDULA; BUTYLPHENYL METHYLPROPIONAL; SORBITOL; SODIUM PYRROLIDONE CARBOXYLATE; GLYCYRRHIZA GLABRA; LINALOOL, (+)-; CITRAL; COUMARIN; .ALPHA.-TOCOPHEROL ACETATE; YUCCA SCHIDIGERA ROOT; VITAMIN A PALMITATE; PHENOXYETHANOL; CHINESE CINNAMON; PROLINE; SANGUISORBA OFFICINALIS ROOT; SERINE; FD&C BLUE NO. 1; GLYCINE; GLUTAMIC ACID; LYSINE; ALANINE; ARGININE; LECITHIN, SOYBEAN; LEVOMENOL; THREONINE; SILICON DIOXIDE; APPLE; COLA ACUMINATA SEED

Acne Treatment Daytime

Active ingredient Purpose

Salicylic Acid (2%) Acne Treatment

Uses

for the treatment of acne

KEEP OUT OF REACH OF CHILDREN

Using other topical acne drugs at the same time or right after use of this product may increase dryness or irritation of the skin. If this occurs, only one drug should be used, unless directed by a doctor

INDICATIONS AND USAGE

Using other topical acne drugs at the same time or right after use of this product may increase dryness or irritation of the skin. If this occurs, only one drug should be used, unless directed by a doctor

Warnings For external use only

Directions

- Cleanse face thoroughly before applying

- apply directly on acne pimples

INACTIVE INGREDIENT

Water (Aqua), Alcohol, Butylene Glycol, Hamamelis Virginiana (Witch Hazel) water, Lactic Acid, Salicylic Acid, PEG-40 Hydrogenated Castor Oil, PPG-26-Buteth-26, Hydroxyethylcellulose, Sodium C8-16 Isoalkylsuccinyl Soy Sulfonate, Ammonium hydroxide, Farnesol, Fragrance (parfum), Glycerin, Tetra-sodium EDTA, Niacinamide, Panthenol, Lavandula Angustifolia (Lavender) Flower Extract, Camellia Oleifera Leaf Extract, Ascorbic Acid, Echinacea Purpurea Extract, Cymbopogon Schoenanthus Extract, Sodium Hyaluronate, Limonene, Propylene Glycol, Hexyl Cinnamal Epilobium Angustifolium Flower/Leaf/Stem Extract, Hypnea Musciformis Extract, Citronellol, Betaine, Saccharomyces Lysate Extract, Sargassum Filipendula Extract, Butylphenyl Methylpropional, Sorbitol, Saccharomyces/copper ferment, Saccharomyces/Zinc Ferment, Sodium PCA, Saccharomyces/Iron Ferment, Saccharomyces/magnesium Ferment, Glycyrrhiza (Licorice) Root Extract, Saccharomyces/Silicon Ferment, Linalool, Citral, Coumarin, Gellidiela Acerosa Extract, Tocopheryl Acetate, Yucca Schidigera Root Extract, Retinyl Palmitate, Phenoxyethanol, Cinnamomum Cassia Bark Extract, Proline, Poterium Officinale Root Extract, Zingiber Officiale (Ginger) Root Extract, Serine, Blue 1 (CI 42090), Glycine, Glutamic Acid, Lysine, Alanine, Arginine, Lecithin, Bisabolol, Threonine, Silica, Pyrus Malus (Apple) Fruit Extract,Cola Acuminata Seed Extract

PACKAGE LABEL

(Malin+Goetz)

acne treatment daytime

0.5fl. oz. 15 ml